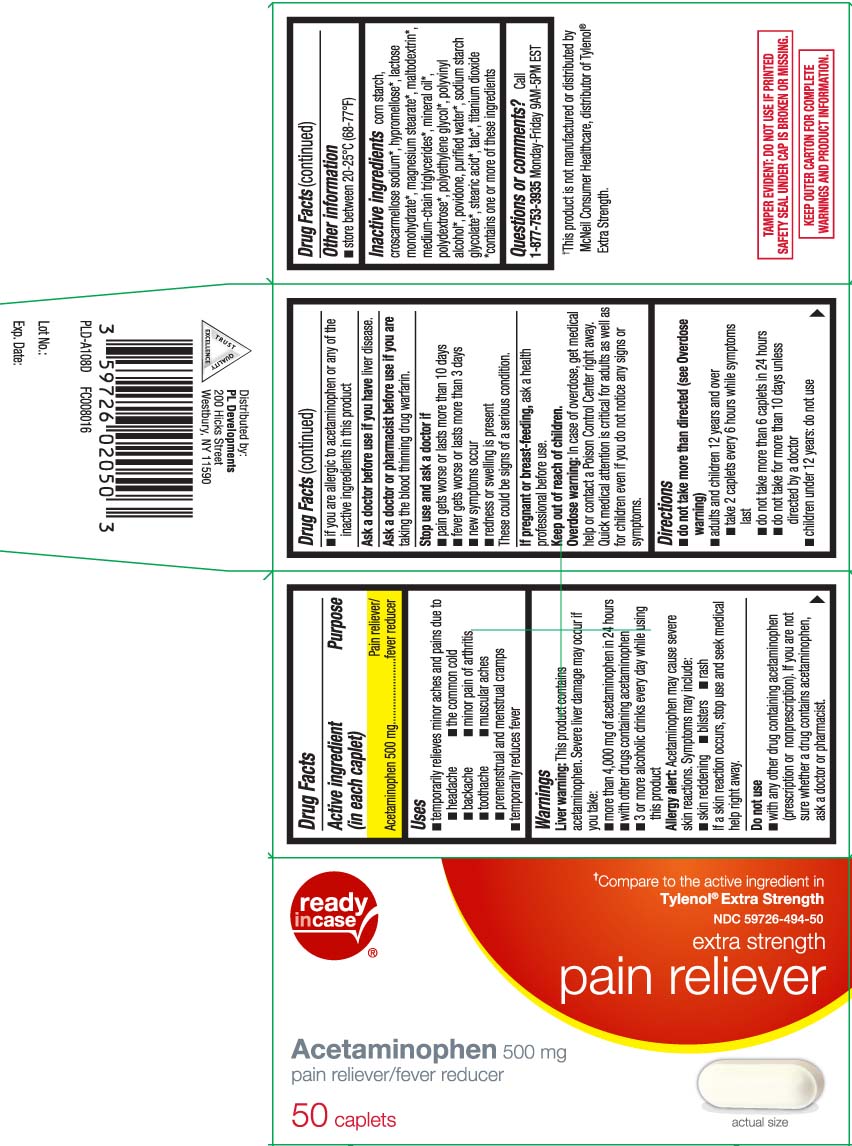 DRUG LABEL: Pain Relief
NDC: 59726-494 | Form: TABLET
Manufacturer: P & L Development, LLC
Category: otc | Type: HUMAN OTC DRUG LABEL
Date: 20250818

ACTIVE INGREDIENTS: ACETAMINOPHEN 500 mg/1 1
INACTIVE INGREDIENTS: STARCH, CORN; CROSCARMELLOSE SODIUM; HYPROMELLOSES; LACTOSE MONOHYDRATE; MAGNESIUM STEARATE; MINERAL OIL; POLYETHYLENE GLYCOL, UNSPECIFIED; POVIDONE; WATER; SODIUM STARCH GLYCOLATE TYPE A CORN; STEARIC ACID; TALC; TITANIUM DIOXIDE; POLYVINYL ALCOHOL, UNSPECIFIED; MALTODEXTRIN; MEDIUM-CHAIN TRIGLYCERIDES; POLYDEXTROSE

Drug Facts

Active ingredient (in each caplet)

Acetaminophen 500 mg

Purpose

Pain reliever/fever reducer

Uses

- temporarily relieves minor aches and pains due to:
  - headache
  - the common cold
  - backache
  - minor pain of arthritis
  - toothache
  - muscular aches
  - premenstrual and menstrual cramps
- temporarily reduces fever

Warnings

Liver warning: This product contains acetaminophen. Severe liver damage may occur if you take:

- more than 4,000 mg of acetaminophen in 24 hours
- with other drugs containing acetaminophen
- 3 or more alcoholic drinks ever day while using this product

Allergy alert: Acetaminophen may cause severe skin reactions. Symptoms may include:

- skin reddening
- blisters
- rash

If a skin reaction occurs, stop use and seek a medical help right away.

Do not use

- with any other drug containing acetaminophen (prescription or nonprescription). If you are not sure whether a drug contains acetaminophen, ask a doctor or pharmacist.
- if you are allergic to acetaminophen or any of the inactive ingredients in this product

Ask a doctor before use if you have

liver disease.

Ask a doctor or pharmacist before use if you are

taking the blood thinning drug warfarin.

Stop use and ask a doctor if

- pain gets worse or lasts more than 10 days
- fever gets worse or lasts more than 3 days
- new symptoms occur
- redness or swelling is present

These could be signs of a serious condition.

If pregnant or breast-feeding,

ask a health professional before use.

Keep out of reach of children.

Overdose warning: In case of overdose, get medical help or contact a Poison Control Center right away. Quick medical attention is critical for adults as well as for children even if you do not notice any signs or symptoms.

Directions

- do not take more than directed (see Overdose warning)
- adults and children 12 years and over
  - take 2 caplets every 6 hours while symptoms last
  - do not take more than 6 caplets in 24 hours
  - do not take for more than 10 days unless directed by a doctor
- children under 12 years: do not use

Other information

- store between 20-25°C (68-77°F)

Inactive ingredients

corn starch, croscarmellose sodium*, hypromellose*, lactose monohydrate*, magnesium stearate*,maltodextrin*, medium-chain triglycerides*, mineral oil*, polydextrose*, polyethylene glycol*, polyvinyl alcohol*, povidone, purified water*, sodium starch glycolate, stearic acid*, talc*, titanium dioxide

*contains one or more of these ingredients

Questions or comments?

Call 1-877-753-3935 Monday-Friday 9AM-5PM EST

Principal Display Panel

Compare to the active ingredient in Tylenol® Extra Strength†

Extra Strength

Pain Reliever

Acetaminophen, 500 mg

Pain Reliever/Fever Reducer

Caplets

†This product is not manufactured or distributed by McNeil Consumer Healthcare, distributor of Tylenol® Extra Strength.

KEEP OUTER CARTON FOR COMPLETE WARNINGS AND PRODUCT INFORMATION.

TAMPER EVIDENT: DO NOT USE IF PRINTED SAFETY SEAL UNDER CAP IS BROKEN OR MISSING.

Distributed by:

PL Developments

200 Hicks Street

Westbury, NY 11590

Product Label

READYinCASE Pain Reliever